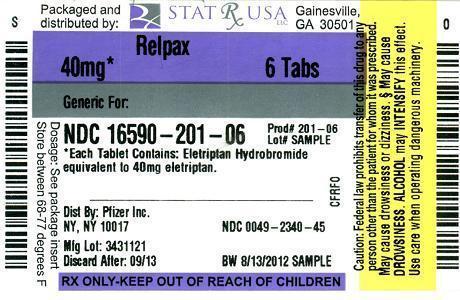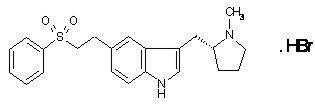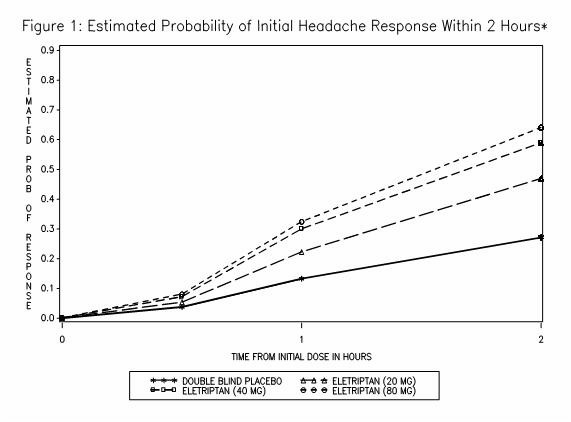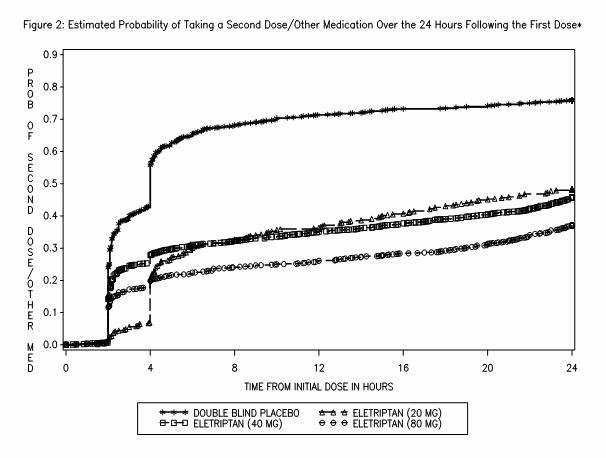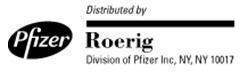 DRUG LABEL: Relpax
NDC: 16590-201 | Form: TABLET, FILM COATED
Manufacturer: STAT Rx USA LLC
Category: prescription | Type: HUMAN PRESCRIPTION DRUG LABEL
Date: 20120813

ACTIVE INGREDIENTS: eletriptan hydrobromide 40 mg/1 1
INACTIVE INGREDIENTS: cellulose, microcrystalline; lactose; croscarmellose sodium; magnesium stearate; titanium dioxide; hypromelloses; triacetin; FD&C YELLOW NO. 6; Aluminum Oxide

RELPAX® (eletriptan hydrobromide) Tablets

DESCRIPTION

RELPAX® (eletriptan) Tablets contain eletriptan hydrobromide, which is a selective 5-hydroxytryptamine 1B/1D (5-HT1B/1D) receptor agonist. Eletriptan is chemically designated as (R)-3-[(1-Methyl-2-pyrrolidinyl)methyl]-5-[2-(phenylsulfonyl)ethyl]-1H-indole monohydrobromide, and it has the following chemical structure:

The empirical formula is C22H26N2O2S . HBr, representing a molecular weight of 463.40. Eletriptan hydrobromide is a white to light pale colored powder that is readily soluble in water.

Each RELPAX Tablet for oral administration contains 24.2 or 48.5 mg of eletriptan hydrobromide equivalent to 20 mg or 40 mg of eletriptan, respectively. Each tablet also contains the inactive ingredients microcrystalline cellulose NF, lactose NF, croscarmellose sodium NF, magnesium stearate NF, titanium dioxide USP, hypromellose, triacetin USP and FD&C Yellow No. 6 aluminum lake.

CLINICAL PHARMACOLOGY

Mechanism of Action

Eletriptan binds with high affinity to 5-HT1B, 5-HT1D and 5-HT1F receptors, has modest affinity for 5-HT1A, 5-HT1E, 5-HT2B and 5-HT7 receptors, and little or no affinity for 5-HT2A, 5-HT2C, 5-HT3, 5-HT4, 5-HT5A and 5-HT6 receptors. Eletriptan has no significant affinity or pharmacological activity at adrenergic alpha1, alpha2, or beta; dopaminergic D1 or D2; muscarinic; or opioid receptors.

Two theories have been proposed to explain the efficacy of 5-HT receptor agonists in migraine. One theory suggests that activation of 5-HT1 receptors located on intracranial blood vessels, including those on the arteriovenous anastomoses, leads to vasoconstriction, which is correlated with the relief of migraine headache. The other hypothesis suggests that activation of 5-HT1 receptors on sensory nerve endings in the trigeminal system results in the inhibition of pro-inflammatory neuropeptide release.

In the anesthetized dog, eletriptan has been shown to reduce carotid arterial blood flow, with only a small increase in arterial blood pressure at high doses. While the effect on blood flow was selective for the carotid arterial bed, decreases in coronary artery diameter were observed. Eletriptan has also been shown to inhibit trigeminal nerve activity in the rat.

Pharmacokinetics

Absorption

Eletriptan is well absorbed after oral administration with peak plasma levels occurring approximately 1.5 hours after dosing to healthy subjects. In patients with moderate to severe migraine the median Tmax is 2.0 hours. The mean absolute bioavailability of eletriptan is approximately 50%. The oral pharmacokinetics are slightly more than dose-proportional over the clinical dose range. The AUC and Cmax of eletriptan are increased by approximately 20 to 30% following oral administration with a high fat meal.

Distribution

The volume of distribution of eletriptan following IV administration is 138L. Plasma protein binding is moderate and approximately 85%.

Metabolism

The N-demethylated metabolite of eletriptan is the only known active metabolite. This metabolite causes vasoconstriction similar to eletriptan in animal models. Though the half-life of the metabolite is estimated to be about 13 hours, the plasma concentration of the N-demethylated metabolite is 10–20% of parent drug and is unlikely to contribute significantly to the overall effect of the parent compound.

In vitro studies indicate that eletriptan is primarily metabolized by cytochrome P-450 enzyme CYP3A4 (see WARNINGS, DOSAGE AND ADMINISTRATION and CLINICAL PHARMACOLOGY: Drug Interactions).

Elimination

The terminal elimination half-life of eletriptan is approximately 4 hours. Mean renal clearance (CLR) following oral administration is approximately 3.9 L/h. Non-renal clearance accounts for about 90% of the total clearance.

Special Populations

Age

The pharmacokinetics of eletriptan are generally unaffected by age.

Eletriptan has been given to only 50 patients over the age of 65. Blood pressure was increased to a greater extent in elderly subjects than in young subjects. The pharmacokinetic disposition of eletriptan in the elderly is similar to that seen in younger adults (see PRECAUTIONS).

There is a statistically significant increased half-life (from about 4.4 hours to 5.7 hours) between elderly (65 to 93 years of age) and younger adult subjects (18 to 45 years of age) (see PRECAUTIONS).

Gender

The pharmacokinetics of eletriptan are unaffected by gender.

Race

A comparison of pharmacokinetic studies run in western countries with those run in Japan has indicated an approximate 35% reduction in the exposure of eletriptan in Japanese male volunteers compared to western males. Population pharmacokinetic analysis of two clinical studies indicates no evidence of pharmacokinetic differences between Caucasians and non-Caucasian patients.

Menstrual Cycle

In a study of 16 healthy females, the pharmacokinetics of eletriptan remained consistent throughout the phases of the menstrual cycle.

Renal Impairment

There was no significant change in clearance observed in subjects with mild, moderate or severe renal impairment, though blood pressure elevations were observed in this population (see WARNINGS).

Hepatic Impairment

The effects of severe hepatic impairment on eletriptan metabolism have not been evaluated. Subjects with mild or moderate hepatic impairment demonstrated an increase in both AUC (34%) and half-life. The Cmax was increased by 18% (see PRECAUTIONS and DOSAGE AND ADMINISTRATION).

Drug Interactions

CYP3A4 inhibitors

In vitro studies have shown that eletriptan is metabolized by the CYP3A4 enzyme. A clinical study demonstrated about a 3-fold increase in Cmax and about a 6-fold increase in the AUC of eletriptan when combined with ketoconazole. The half-life increased from 5 hours to 8 hours and the Tmax increased from 2.8 hours to 5.4 hours. Another clinical study demonstrated about a 2-fold increase in Cmax and about a 4-fold increase in AUC when erythromycin was co-administered with eletriptan. It has also been shown that co-administration of verapamil and eletriptan yields about a 2-fold increase in Cmax and about a 3-fold increase in AUC of eletriptan, and that co-administration of fluconazole and eletriptan yields about a 1.4-fold increase in Cmax and about a 2-fold increase in AUC of eletriptan.

Eletriptan should not be used within at least 72 hours of treatment with the following potent CYP3A4 inhibitors: ketoconazole, itraconazole, nefazodone, troleandomycin, clarithromycin, ritonavir and nelfinavir. Eletriptan should not be used within 72 hours with drugs that have demonstrated potent CYP3A4 inhibition and have this potent effect described in the CONTRAINDICATIONS, WARNINGS or PRECAUTIONS sections of their labeling (see WARNINGS and DOSAGE AND ADMINISTRATION).

Propranolol

The Cmax and AUC of eletriptan were increased by 10 and 33%, respectively, in the presence of propranolol. No interactive increases in blood pressure were observed. No dosage adjustment appears to be needed for patients taking propranolol (see PRECAUTIONS).

The effect of eletriptan on other drugs

The effect of eletriptan on enzymes other than cytochrome P-450 has not been investigated. In vitro human liver microsome studies suggest that eletriptan has little potential to inhibit CYP1A2, 2C9, 2E1 and 3A4 at concentrations up to 100µM. While eletriptan has an effect on CYP2D6 at high concentration, this effect should not interfere with metabolism of other drugs when eletriptan is used at recommended doses. There is no in vitro or in vivo evidence that clinical doses of eletriptan will induce drug metabolizing enzymes. Therefore, eletriptan is unlikely to cause clinically important drug interactions mediated by these enzymes.

CLINICAL STUDIES

The efficacy of RELPAX in the acute treatment of migraines was evaluated in eight randomized, double-blind placebo-controlled studies. All eight studies used 40 mg. Seven studies evaluated an 80 mg dose and two studies included a 20 mg dose.

In all eight studies, randomized patients treated their headaches as outpatients. Seven studies enrolled adults and one study enrolled adolescents (age 11 to 17). Patients treated in the seven adult studies were predominantly female (85%) and Caucasian (94%) with a mean age of 40 years (range 18 to 78). In all studies, patients were instructed to treat a moderate to severe headache. Headache response, defined as a reduction in headache severity from moderate or severe pain to mild or no pain, was assessed up to 2 hours after dosing. Associated symptoms such as nausea, vomiting, photophobia and phonophobia were also assessed.

Maintenance of response was assessed for up to 24 hours post dose. In the adult studies, a second dose of RELPAX Tablets or other medication was allowed 2 to 24 hours after the initial treatment for both persistent and recurrent headaches. The incidence and time to use of these additional treatments were also recorded.

In the seven adult studies, the percentage of patients achieving headache response 2 hours after treatment was significantly greater among patients receiving RELPAX Tablets at all doses compared to those who received placebo. The two-hour response rates from these controlled clinical studies are summarized in Table 1.

Table 1: Percentage of Patients with Headache Response (Mild or No Headache) 2 Hours Following Treatment
 | Placebo | RELPAX 20 mg | RELPAX 40 mg | RELPAX 80 mg
Study 1 | 23.8% (n=126) | 54.3% [p value < 0.05 vs placebo] (n=129) | 65.0% (n=117) | 77.1% (n=118)
Study 2 | 19.0% (n=232) | NA | 61.6% (n=430) | 64.6% (n=446)
Study 3 | 21.7% (n=276) | 47.3% (n=273) | 61.9% (n=281) | 58.6% (n=290)
Study 4 | 39.5% (n=86) | NA | 62.3% (n=175) | 70.0% (n=170)
Study 5 | 20.6% (n=102) | NA | 53.9% (n=206) | 67.9% (n=209)
Study 6 | 31.3% (n=80) | NA | 63.9% (n=169) | 66.9% (n=160)
Study 7 | 29.5% (n=122) | NA | 57.5% (n=492) | NA
NA - Not Applicable

Comparisons of the performance of different drugs based upon results obtained in different clinical trials are never reliable. Because studies are generally conducted at different times, with different samples of patients, by different investigators, employing different criteria and/or different interpretations of the same criteria, under different conditions (dose, dosing regimen, etc.), quantitative estimates of treatment response and the timing of response may be expected to vary considerably from study to study.

The estimated probability of achieving an initial headache response within 2 hours following treatment is depicted in Figure 1.

*Figure 1 shows the Kaplan-Meier plot of probability over time of obtaining headache response (no or mild pain) following treatment with eletriptan. The plot is based on 7 placebo-controlled, outpatient trials in adults providing evidence of efficacy (Studies 1 through 7). Patients not achieving headache response or taking additional treatment prior to 2 hours were censored at 2 hours.

For patients with migraine-associated photophobia, phonophobia, and nausea at baseline, there was a decreased incidence of these symptoms following administration of RELPAX as compared to placebo.

Two to 24 hours following the initial dose of study treatment, patients were allowed to use additional treatment for pain relief in the form of a second dose of study treatment or other medication. The estimated probability of taking a second dose or other medications for migraine over the 24 hours following the initial dose of study treatment is summarized in Figure 2.

*This Kaplan-Meier plot is based on data obtained in 7 placebo-controlled trials in adults (Studies 1 through 7). Patients were instructed to take a second dose of study medication as follows: a) in the event of no response at 2 hours (studies 2 and 4–7) or at 4 hours (study 3); b) in the event of headache recurrence within 24 hours (studies 2–7). Patients not using additional treatments were censored at 24 hours. The plot includes both patients who had headache response at 2 hours and those who had no response to the initial dose. It should be noted that the protocols did not allow remedication within 2 hours post dose.

The efficacy of RELPAX was unaffected by the duration of attack; gender or age of the patient; relationship to menses; or concomitant use of estrogen replacement therapy/oral contraceptives or frequently used migraine prophylactic drugs.

In a single study in adolescents (n=274), there were no statistically significant differences between treatment groups. The headache response rate at 2 hours was 57% for both RELPAX 40 mg Tablets and placebo.

INDICATIONS AND USAGE

RELPAX is indicated for the acute treatment of migraine with or without aura in adults.

RELPAX is not intended for the prophylactic therapy of migraine or for use in the management of hemiplegic or basilar migraine (see CONTRAINDICATIONS). Safety and effectiveness of RELPAX Tablets have not been established for cluster headache, which is present in an older, predominantly male population.

CONTRAINDICATIONS

RELPAX Tablets should not be given to patients with ischemic heart disease (e.g., angina pectoris, history of myocardial infarction, or documented silent ischemia) or to patients who have symptoms, or findings consistent with ischemic heart disease, coronary artery vasospasm, including Prinzmetal's variant angina, or other significant underlying cardiovascular disease (see WARNINGS).

RELPAX Tablets should not be given to patients with cerebrovascular syndromes including (but not limited to) strokes of any type as well as transient ischemic attacks (see WARNINGS).

RELPAX Tablets should not be given to patients with peripheral vascular disease including (but not limited to) ischemic bowel disease (see WARNINGS).

Because RELPAX Tablets may increase blood pressure, it should not be given to patients with uncontrolled hypertension (see WARNINGS).

RELPAX Tablets should not be administered to patients with hemiplegic or basilar migraine.

RELPAX Tablets should not be used within 24 hours of treatment with another 5-HT1 agonist, an ergotamine-containing or ergot-type medication such as dihydroergotamine (DHE) or methysergide.

RELPAX Tablets should not be used in patients with known hypersensitivity to eletriptan or any of its inactive ingredients.

RELPAX Tablets should not be given to patients with severe hepatic impairment.

WARNINGS

RELPAX Tablets should only be used where a clear diagnosis of migraine has been established.

CYP3A4 Inhibitors

Eletriptan should not be used within at least 72 hours of treatment with the following potent CYP3A4 inhibitors: ketoconazole, itraconazole, nefazodone, troleandomycin, clarithromycin, ritonavir, and nelfinavir. Eletriptan should not be used within 72 hours with drugs that have demonstrated potent CYP3A4 inhibition and have this potent effect described in the CONTRAINDICATIONS, WARNINGS or PRECAUTIONS sections of their labeling (see CLINICAL PHARMACOLOGY: Drug Interactions and DOSAGE AND ADMINISTRATION).

In a coronary angiographic study of rapidly infused intravenous eletriptan to concentrations exceeding those achieved with 80 mg oral eletriptan in the presence of potent CYP3A4 inhibitors, a small dose-related decrease in coronary artery diameter similar to that seen with a 6 mg subcutaneous dose of sumatriptan was observed.

Risk of Myocardial Ischemia and/or Infarction and Other Cardiac Events

Because of the potential of 5-HT1 agonists to cause coronary vasospasm, eletriptan should not be given to patients with documented ischemic or vasospastic coronary artery disease (CAD) (see CONTRAINDICATIONS). It is strongly recommended that eletriptan not be given to patients in whom unrecognized CAD is predicted by the presence of risk factors (e.g., hypertension, hypercholesterolemia, smoker, obesity, diabetes, strong family history of CAD, female with surgical or physiological menopause, or male over 40 years of age) unless a cardiovascular evaluation provides satisfactory clinical evidence that the patient is reasonably free of coronary artery and ischemic myocardial disease or other significant underlying cardiovascular disease. The sensitivity of cardiac diagnostic procedures to detect cardiovascular disease or predisposition to coronary artery vasospasm is modest, at best. If, during the cardiovascular evaluation, the patient's medical history, electrocardiographic, or other investigations reveal findings indicative of, or consistent with coronary artery vasospasm or myocardial ischemia, eletriptan should not be administered (see CONTRAINDICATIONS).

For patients with risk factors predictive of CAD, who are determined to have a satisfactory cardiovascular evaluation, it is strongly recommended that administration of the first dose of eletriptan take place in the setting of a physician's office or similar medically staffed and equipped facility unless the patient has previously received eletriptan. Because cardiac ischemia can occur in the absence of clinical symptoms, consideration should be given to obtaining on the first occasion of use an electrocardiogram (ECG) during the interval immediately following administration of RELPAX Tablets, in these patients with risk factors.

It is recommended that patients who are intermittent long-term users of 5-HT1 agonists including RELPAX Tablets, and who have or acquire risk factors predictive of CAD, as described above, undergo periodic cardiovascular evaluation as they continue to use RELPAX Tablets.

The systematic approach described above is intended to reduce the likelihood that patients with unrecognized cardiovascular disease will be inadvertently exposed to eletriptan.

Cardiac Events and Fatalities

Serious adverse cardiac events, including acute myocardial infarction, life-threatening disturbances of cardiac rhythm, and death have been reported within a few hours following the administration of 5-HT1 agonists including RELPAX. Considering the extent of use of 5-HT1 agonists in patients with migraine, the incidence of these events is extremely low.

Premarketing experience with eletriptan among the 7,143 unique individuals who received eletriptan during premarketing clinical trials: In a clinical pharmacology study, in subjects undergoing diagnostic coronary angiography, a subject with a history of angina, hypertension and hypercholesterolemia, receiving intravenous eletriptan (Cmax of 127 ng/mL equivalent to 60 mg oral eletriptan), reported chest tightness and experienced angiographically documented coronary vasospasm with no ECG changes of ischemia.

There was also one report of atrial fibrillation in a patient with a past history of atrial fibrillation.

Postmarketing experience with eletriptan: Serious cardiovascular events, some resulting in death, have been reported in association with the use of RELPAX. In very rare cases, these events have occurred in the absence of known cardiovascular diseases. The uncontrolled nature of postmarketing surveillance, however, makes it impossible to determine definitively if the cases were actually caused by eletriptan or to reliably assess causation in individual cases.

Cerebrovascular Events and Fatalities Associated With 5-HT1 Agonists

Cerebral hemorrhage, subarachnoid hemorrhage, stroke, and other cerebrovascular events have been reported in patients treated with 5-HT1 agonists, and some have resulted in fatalities. In a number of cases, it appears possible that the cerebrovascular events were primary, the agonist having been administered in the incorrect belief that the symptoms experienced were a consequence of migraine, when they were not. It should be noted that patients with migraine may be at increased risk of certain cerebrovascular events (e.g., stroke, hemorrhage, and transient ischemic attack).

Other Vasospasm-Related Events

5-HT1 agonists may cause vasospastic reactions other than coronary artery vasospasm. Both peripheral vascular ischemia and colonic ischemia with abdominal pain and bloody diarrhea have been reported with 5-HT1 agonists.

Serotonin Syndrome

The development of a potentially life-threatening serotonin syndrome may occur with triptans, including Relpax treatment, particularly during combined use with selective serotonin reuptake inhibitors (SSRIs) or serotonin norepinephrine reuptake inhibitors (SNRIs). If concomitant treatment with Relpax and an SSRI (e.g., fluoxetine, paroxetine, sertraline, fluvoxamine, citalopram, escitalopram) or SNRI (e.g., venlafaxine, duloxetine) is clinically warranted, careful observation of the patient is advised, particularly during treatment initiation and dose increases. Serotonin syndrome symptoms may include mental status changes (e.g., agitation, hallucinations, coma), autonomic instability (e.g., tachycardia, labile blood pressure, hyperthermia), neuromuscular aberrations (e.g., hyperreflexia, incoordination) and/or gastrointestinal symptoms (e.g., nausea, vomiting, diarrhea). (See PRECAUTIONS—DRUG INTERACTIONS).

Increase in Blood Pressure

Significant elevation in blood pressure, including hypertensive crisis, has been reported on rare occasions in patients receiving 5-HT1 agonists with and without a history of hypertension. In clinical pharmacology studies, oral eletriptan (at doses of 60 mg or more) was shown to cause small, transient dose-related increases in blood pressure, predominantly diastolic, consistent with its mechanism of action and with other 5-HT1B/1D agonists. The effect was more pronounced in renally impaired and elderly subjects. A single patient with hepatic cirrhosis received eletriptan 80 mg and experienced a blood pressure of 220/96 mm Hg five hours after dosing. The treatment-related event persisted for seven hours.

Eletriptan is contraindicated in patients with uncontrolled hypertension (see CONTRAINDICATIONS).

An 18% increase in mean pulmonary artery pressure was seen following dosing with another 5-HT1 agonist in a study evaluating subjects undergoing cardiac catheterization.

PRECAUTIONS

General

As with other 5-HT1 agonists, sensations of tightness, pain, pressure and heaviness have been reported after treatment with eletriptan in the precordium, throat, and jaw. Events that are localized to the chest, throat, neck and jaw have not been associated with arrhythmias or ischemic ECG changes in clinical trials; in a clinical pharmacology study of subjects undergoing diagnostic coronary angiography, one subject with a history of angina, hypertension and hypercholesterolemia, receiving intravenous eletriptan, reported chest tightness and experienced angiographically documented coronary vasospasm with no ECG changes of ischemia. Because 5-HT1 agonists may cause coronary artery vasospasm, patients who experience signs or symptoms suggestive of angina following dosing should be evaluated for the presence of CAD or a predisposition to Prinzmetal's variant angina before receiving additional doses of medication, and should be monitored electrocardiographically if dosing is resumed and similar symptoms recur. Similarly, patients who experience other symptoms or signs suggestive of decreased arterial flow, such as ischemic bowel syndrome or Raynaud's syndrome following the use of any 5-HT1 agonist are candidates for further evaluation (see CONTRAINDICATIONS and WARNINGS).

Overuse

Excessive use of any anti-migraine medicinal product can lead to daily chronic headaches. Overuse of all triptans has been reported primarily in patients with chronic daily headache.

Hepatically Impaired Patients

The effects of severe hepatic impairment on eletriptan metabolism was not evaluated. Subjects with mild or moderate hepatic impairment demonstrated an increase in both AUC (34%) and half-life. The Cmax was increased by 18%. Eletriptan should not be used in patients with severe hepatic impairment. No dose adjustment is necessary in mild to moderate impairment (see DOSAGE AND ADMINISTRATION).

Binding to Melanin-Containing Tissues

In rats treated with a single intravenous (3 mg/kg) dose of radio-labeled eletriptan, elimination of radioactivity from the retina was prolonged, suggesting that eletriptan and/or its metabolites may bind to the melanin of the eye. Because there could be accumulation in melanin-rich tissues over time, this raises the possibility that eletriptan could cause toxicity in these tissues after extended use. Although no systematic monitoring of ophthalmologic function was undertaken in clinical trials, and no specific recommendations for ophthalmologic monitoring are offered, prescribers should be aware of the possibility of long-term ophthalmologic effects.

Corneal Opacities

Transient corneal opacities were seen in dogs receiving oral eletriptan at 5 mg/kg and above. They were observed during the first week of treatment, but were not present thereafter despite continued treatment. Exposure at the no-effect dose level of 2.5 mg/kg was approximately equal to that achieved in humans at the maximum recommended daily dose.

Information for Patients

See PATIENT INFORMATION at the end of this labeling for the text of the separate leaflet provided for patients.

Patients should be cautioned about the risk of serotonin syndrome with the use of RELPAX or other triptans, especially during combined use with selective serotonin reuptake inhibitors (SSRIs) or serotonin norepinephrine reuptake inhibitors (SNRIs).

Laboratory Tests

No specific laboratory tests are recommended.

Drug Interactions

Ergot-containing drugs have been reported to cause prolonged vasospastic reactions. Because these effects may be additive, use of ergotamine-containing or ergot-type medications (like dihydroergotamine [DHE] or methysergide) and eletriptan within 24 hours of each other is not recommended (see CONTRAINDICATIONS).

CYP3A4 Inhibitors

Eletriptan is metabolized primarily by CYP3A4 (see WARNINGS regarding use with potent CYP3A4 inhibitors).

Monoamine Oxidase Inhibitors

Eletriptan is not a substrate for monoamine oxidase (MAO) enzymes; therefore, there is no expectation of an interaction between eletriptan and MAO inhibitors.

Propranolol

The Cmax and AUC of eletriptan were increased by 10 and 33% respectively in the presence of propranolol. No interactive increases in blood pressure were observed. No dosage adjustment appears to be needed for patients taking propranolol (see CLINICAL PHARMACOLOGY).

Selective Serotonin Reuptake Inhibitors/Serotonin Norepinephrine Reuptake Inhibitors and Serotonin Syndrome

Cases of life-threatening serotonin syndrome have been reported during combined use of selective serotonin reuptake inhibitors (SSRIs) or serotonin norepinephrine reuptake inhibitors (SNRIs) and triptans (See WARNINGS).

Other 5-HT1 agonists

Concomitant use of other 5-HT1 agonists within 24 hours of RELPAX treatment is not recommended (see CONTRAINDICATIONS).

Drug/Laboratory Test Interactions

RELPAX Tablets are not known to interfere with commonly employed clinical laboratory tests.

Carcinogenesis

Lifetime carcinogenicity studies, 104 weeks in duration, were carried out in mice and rats by administering eletriptan in the diet. In rats, the incidence of testicular interstitial cell adenomas was increased at the high dose of 75 mg/kg/day. The estimated exposure (AUC) to parent drug at that dose was approximately 6 times that achieved in humans receiving the maximum recommended daily dose (MRDD) of 80 mg, and at the no-effect dose of 15 mg/kg/day it was approximately 2 times the human exposure at the MRDD. In mice, the incidence of hepatocellular adenomas was increased at the high dose of 400 mg/kg/day. The exposure to parent drug (AUC) at that dose was approximately 18 times that achieved in humans receiving the MRDD, and the AUC at the no-effect dose of 90 mg/kg/day was approximately 7 times the human exposure at the MRDD.

Mutagenesis

Eletriptan was not mutagenic in bacterial or mammalian cell assays in vitro, testing negative in the Ames reverse mutation test and the hypoxanthine-guanine phosphoribosyl transferase (HGPRT) mutation test in Chinese hamster ovary cells. It was not clastogenic in two in vivo mouse micronucleus assays. Results were equivocal in in vitro human lymphocyte clastogenicity tests, in which the incidence of polyploidy was increased in the absence of metabolic activation (-S9 conditions), but not in the presence of metabolic activation.

Impairment of Fertility

In a rat fertility and early embryonic development study, doses tested were 50, 100 and 200 mg/kg/day, resulting in systemic exposures to parent drug in rats, based on AUC, that were 4, 8 and 16 times MRDD, respectively, in males and 7, 14 and 28 times MRDD, respectively, in females. There was a prolongation of the estrous cycle at the 200 mg/kg/day dose due to an increase in duration of estrus, based on vaginal smears. There were also dose-related, statistically significant decreases in mean numbers of corpora lutea per dam at all 3 doses, resulting in decreases in mean numbers of implants and viable fetuses per dam. This suggests a partial inhibition of ovulation by eletriptan. There was no effect on fertility of males and no other effect on fertility of females.

Pregnancy

Pregnancy Category C

In reproductive toxicity studies in rats and rabbits, oral administration of eletriptan was associated with developmental toxicity (decreased fetal and pup weights and an increased incidence of fetal structural abnormalities). Effects on fetal and pup weights were observed at doses that were, on a mg/m^2 basis, 6 to 12 times greater than the clinical maximum recommended daily dose (MRDD) of 80 mg. The increase in structural alterations occurred in the rat and rabbit at doses that, on a mg/m^2 basis, were 12 times greater than (rat) and approximately equal to (rabbit) the MRDD.

When pregnant rats were administered eletriptan during the period of organogenesis at doses of 10, 30 or 100 mg/kg/day, fetal weights were decreased and the incidences of vertebral and sternebral variations were increased at 100 mg/kg/day (approximately 12 times the MRDD on a mg/m^2 basis). The 100 mg/kg dose was also maternally toxic, as evidenced by decreased maternal body weight gain during gestation. The no-effect dose for developmental toxicity in rats exposed during organogenesis was 30 mg/kg, which is approximately 4 times the MRDD on a mg/m^2 basis.

When doses of 5, 10 or 50 mg/kg/day were given to New Zealand White rabbits throughout organogenesis, fetal weights were decreased at 50 mg/kg, which is approximately 12 times the MRDD on a mg/m^2 basis. The incidences of fused sternebrae and vena cava deviations were increased in all treated groups. Maternal toxicity was not produced at any dose. A no-effect dose for developmental toxicity in rabbits exposed during organogenesis was not established, and the 5 mg/kg dose is approximately equal to the MRDD on a mg/m^2 basis.

There are no adequate and well-controlled studies in pregnant women; therefore, eletriptan should be used during pregnancy only if the potential benefit justifies the potential risk to the fetus.

Nursing Mothers

Eletriptan is excreted in human breast milk. In one study of 8 women given a single dose of 80 mg, the mean total amount of eletriptan in breast milk over 24 hours in this group was approximately 0.02% of the administered dose. The ratio of eletriptan mean concentration in breast milk to plasma was 1:4, but there was great variability. The resulting eletriptan concentration-time profile was similar to that seen in the plasma over 24 hours, with very low concentrations of drug (mean 1.7 ng/mL) still present in the milk 18–24 hours post dose. The N-desmethyl active metabolite was not measured in the breast milk. Caution should be exercised when RELPAX is administered to nursing women.

Pediatric Use

Safety and effectiveness of RELPAX Tablets in pediatric patients have not been established; therefore, RELPAX is not recommended for use in patients under 18 years of age.

The efficacy of RELPAX Tablets (40 mg) in patients 11–17 was not established in a randomized, placebo-controlled trial of 274 adolescent migraineurs (see CLINICAL STUDIES). Adverse events observed were similar in nature to those reported in clinical trials in adults. Postmarketing experience with other triptans includes a limited number of reports that describe pediatric patients who have experienced clinically serious adverse events that are similar in nature to those reported rarely in adults. Long-term safety of eletriptan was studied in 76 adolescent patients who received treatment for up to one year. A similar profile of adverse events to that of adults was observed. The long-term safety of eletriptan in pediatric patients has not been established.

Geriatric Use

Eletriptan has been given to only 50 patients over the age of 65. Blood pressure was increased to a greater extent in elderly subjects than in young subjects. The pharmacokinetic disposition of eletriptan in the elderly is similar to that seen in younger adults (see CLINICAL PHARMACOLOGY). In clinical trials, there were no apparent differences in efficacy or the incidence of adverse events between patients under 65 years of age and those 65 and above (n=50).

There is a statistically significantly increased half-life (from about 4.4 hours to 5.7 hours) between elderly (65 to 93 years of age) and younger adult subjects (18 to 45 years of age) (see CLINICAL PHARMACOLOGY).

ADVERSE REACTIONS

Serious cardiac events, including some that have been fatal, have occurred following the use of 5-HT1 agonists including RELPAX. These events are extremely rare and most have been reported in patients with risk factors predictive of CAD. Events reported have included coronary artery vasospasm, transient myocardial ischemia, myocardial infarction, ventricular tachycardia, and ventricular fibrillation (see CONTRAINDICATIONS, WARNINGS and PRECAUTIONS).

Incidence in Controlled Clinical Trials

Among 4,597 patients who treated the first migraine headache with RELPAX in short-term placebo-controlled trials, the most common adverse events reported with treatment with RELPAX were asthenia, nausea, dizziness, and somnolence. These events appear to be dose-related.

In long-term open-label studies where patients were allowed to treat multiple migraine attacks for up to 1 year, 128 (8.3%) out of 1,544 patients discontinued treatment due to adverse events.

Table 2 lists adverse events that occurred in the subset of 5,125 migraineurs who received eletriptan doses of 20 mg, 40 mg and 80 mg or placebo in worldwide placebo-controlled clinical trials. The events cited reflect experience gained under closely monitored conditions of clinical trials in a highly selected patient population. In actual clinical practice or in other clinical trials, those frequency estimates may not apply, as the conditions of use, reporting behavior, and the kinds of patients treated may differ.

Only adverse events that were more frequent in a RELPAX treatment group compared to the placebo group with an incidence greater than or equal to 2% are included in Table 2.

Table 2: Adverse Experience Incidence in Placebo-Controlled Migraine Clinical Trials: Events Reported by ≥ 2% Patients Treated with RELPAX and More Than Placebo
Adverse Event Type | Placebo (n=988) | RELPAX 20 mg (n=431) | RELPAX 40 mg (n=1774) | RELPAX 80 mg (n=1932)
ATYPICAL SENSATIONS
Paresthesia | 2% | 3% | 3% | 4%
Flushing/feeling of warmth | 2% | 2% | 2% | 2%
PAIN AND PRESSURE SENSATIONS
Chest – tightness/pain/pressure | 1% | 1% | 2% | 4%
Abdominal – pain/discomfort/stomach pain/cramps/pressure | 1% | 1% | 2% | 2%
DIGESTIVE
Dry mouth | 2% | 2% | 3% | 4%
Dyspepsia | 1% | 1% | 2% | 2%
Dysphagia – throat tightness/difficulty swallowing | 0.2% | 1% | 2% | 2%
Nausea | 5% | 4% | 5% | 8%
NEUROLOGICAL
Dizziness | 3% | 3% | 6% | 7%
Somnolence | 4% | 3% | 6% | 7%
Headache | 3% | 4% | 3% | 4%
OTHER
Asthenia | 3% | 4% | 5% | 10%

RELPAX is generally well tolerated. Across all doses, most adverse reactions were mild and transient. The frequency of adverse events in clinical trials did not increase when up to 2 doses of RELPAX were taken within 24 hours. The incidence of adverse events in controlled clinical trials was not affected by gender, age, or race of the patients. Adverse event frequencies were also unchanged by concomitant use of drugs commonly taken for migraine prophylaxis (e.g., SSRIs, beta blockers, calcium channel blockers, tricyclic antidepressants), estrogen replacement therapy and oral contraceptives.

Other Events Observed in Association With the Administration of RELPAX Tablets

In the paragraphs that follow, the frequencies of less commonly reported adverse clinical events are presented. Because the reports include events observed in open studies, the role of RELPAX Tablets in their causation cannot be reliably determined. Furthermore, variability associated with adverse event reporting, the terminology used to describe adverse events, etc., limit the value of the quantitative frequency estimates provided. Event frequencies are calculated as the number of patients reporting an event divided by the total number of patients (N=4,719) exposed to RELPAX. All reported events are included except those already listed in Table 2, those too general to be informative, and those not reasonably associated with the use of the drug. Events are further classified within body system categories and enumerated in order of decreasing frequency using the following definitions: frequent adverse events are those occurring in at least 1/100 patients, infrequent adverse events are those occurring in 1/100 to 1/1000 patients and rare adverse events are those occurring in fewer than 1/1000 patients.

General: Frequent were back pain, chills and pain. Infrequent were face edema and malaise. Rare were abdomen enlarged, abscess, accidental injury, allergic reaction, fever, flu syndrome, halitosis, hernia, hypothermia, lab test abnormal, moniliasis, rheumatoid arthritis and shock.

Cardiovascular: Frequent was palpitation. Infrequent were hypertension, migraine, peripheral vascular disorder and tachycardia. Rare were angina pectoris, arrhythmia, atrial fibrillation, AV block, bradycardia, hypotension, syncope, thrombophlebitis, cerebrovascular disorder, vasospasm and ventricular arrhythmia.

Digestive: Infrequent were anorexia, constipation, diarrhea, eructation, esophagitis, flatulence, gastritis, gastrointestinal disorder, glossitis, increased salivation and liver function tests abnormal. Rare were gingivitis, hematemesis, increased appetite, rectal disorder, stomatitis, tongue disorder, tongue edema and tooth disorder.

Endocrine: Rare were goiter, thyroid adenoma and thyroiditis.

Hemic and Lymphatic: Rare were anemia, cyanosis, leukopenia, lymphadenopathy, monocytosis and purpura.

Immune System Disorders: Allergic reactions, some of which may be serious, including angioedema.

Metabolic: Infrequent were creatine phosphokinase increased, edema, peripheral edema and thirst. Rare were alkaline phosphatase increased, bilirubinemia, hyperglycemia, weight gain and weight loss.

Musculoskeletal: Infrequent were arthralgia, arthritis, arthrosis, bone pain, myalgia and myasthenia. Rare were bone neoplasm, joint disorder, myopathy and tenosynovitis.

Neurological: Frequent were hypertonia, hypesthesia and vertigo. Infrequent were abnormal dreams, agitation, anxiety, apathy, ataxia, confusion, depersonalization, depression, emotional lability, euphoria, hyperesthesia, hyperkinesia, incoordination, insomnia, nervousness, speech disorder, stupor, thinking abnormal and tremor. Rare were abnormal gait, amnesia, aphasia, catatonic reaction, dementia, diplopia, dystonia, hallucinations, hemiplegia, hyperalgesia, hypokinesia, hysteria, manic reaction, neuropathy, neurosis, oculogyric crisis, paralysis, psychotic depression, sleep disorder and twitching.

Respiratory: Frequent was pharyngitis. Infrequent were asthma, dyspnea, respiratory disorder, respiratory tract infection, rhinitis, voice alteration and yawn. Rare were bronchitis, choking sensation, cough increased, epistaxis, hiccup, hyperventilation, laryngitis, sinusitis and sputum increased.

Skin and Appendages: Frequent was sweating. Infrequent were pruritus, rash and skin disorder. Rare were alopecia, dry skin, eczema, exfoliative dermatitis, maculopapular rash, psoriasis, skin discoloration, skin hypertrophy and urticaria.

Special Senses: Infrequent was abnormal vision, conjunctivitis, ear pain, eye pain, lacrimation disorder, photophobia, taste perversion and tinnitus. Rare were abnormality of accommodation, dry eyes, ear disorder, eye hemorrhage, otitis media, parosmia and ptosis.

Urogenital: Infrequent were impotence, polyuria, urinary frequency and urinary tract disorder. Rare were breast pain, kidney pain, leukorrhea, menorrhagia, menstrual disorder and vaginitis.

Other Events Observed During Post-Marketing Use

The following adverse reaction(s) have been identified during postapproval use of RELPAX. Because these reactions are reported voluntarily from a population of uncertain size, it is not always possible to reliably estimate their frequency or establish a causal relationship to drug exposure.

Neurological: seizure

Digestive: vomiting

DRUG ABUSE AND DEPENDENCE

Although the abuse potential of RELPAX has not been assessed, no abuse of, tolerance to, withdrawal from, or drug-seeking behavior was observed in patients who received RELPAX in clinical trials or their extensions. The 5-HT1B/1D agonists, as a class, have not been associated with drug abuse.

OVERDOSAGE

No significant overdoses in premarketing clinical trials have been reported. Volunteers (N=21) have received single doses of 120 mg without significant adverse effects. Daily doses of 160 mg were commonly employed in Phase III trials. Based on the pharmacology of the 5-HT1B/1D agonists, hypertension or other more serious cardiovascular symptoms could occur on overdose.

The elimination half-life of eletriptan is about 4 hours (see CLINICAL PHARMACOLOGY) and therefore monitoring of patients after overdose with eletriptan should continue for at least 20 hours, or longer should symptoms or signs persist.

There is no specific antidote to eletriptan. In cases of severe intoxication, intensive care procedures are recommended, including establishing and maintaining a patent airway, ensuring adequate oxygenation and ventilation, and monitoring and support of the cardiovascular system.

It is unknown what effect hemodialysis or peritoneal dialysis has on the serum concentration of eletriptan.

DOSAGE AND ADMINISTRATION

In controlled clinical trials, single doses of 20 mg and 40 mg were effective for the acute treatment of migraine in adults. A greater proportion of patients had a response following a 40 mg dose than following a 20 mg dose (see CLINICAL STUDIES). Individuals may vary in response to doses of RELPAX Tablets. The choice of dose should therefore be made on an individual basis. An 80 mg dose, although also effective, was associated with an increased incidence of adverse events. Therefore, the maximum recommended single dose is 40 mg.

If after the initial dose, headache improves but then returns, a repeat dose may be beneficial. If a second dose is required, it should be taken at least 2 hours after the initial dose. If the initial dose is ineffective, controlled clinical trials have not shown a benefit of a second dose to treat the same attack. The maximum daily dose should not exceed 80 mg.

The safety of treating an average of more than 3 headaches in a 30-day period has not been established.

CYP3A4 Inhibitors

Eletriptan is metabolized by the CYP3A4 enzyme. Eletriptan should not be used within at least 72 hours of treatment with the following potent CYP3A4 inhibitors: ketoconazole, itraconazole, nefazodone, troleandomycin, clarithromycin, ritonavir and nelfinavir. Eletriptan should not be used within 72 hours with drugs that have demonstrated potent CYP3A4 inhibition and have this potent effect described in the CONTRAINDICATIONS, WARNINGS or PRECAUTIONS sections of their labeling (see WARNINGS and CLINICAL PHARMACOLOGY: Drug Interactions).

Hepatic Impairment

The drug should not be given to patients with severe hepatic impairment since the effect of severe hepatic impairment on eletriptan metabolism was not evaluated. No dose adjustment is necessary in mild to moderate impairment (see CLINICAL PHARMACOLOGY, CONTRAINDICATIONS and PRECAUTIONS).

HOW SUPPLIED

RELPAX 40 mg eletriptan (base) as the hydrobromide, are orange, round, convex shaped, film-coated tablets with debossing - REP40 and Pfizer.

They are supplied as follows:

RELPAX 40 mg - NDC # 16590-201-06

Relabeling by:

STAT Rx USA LLC

Gainesville, GA 30501

STORAGE AND HANDLING

Store at 25°C (77°F); excursions permitted to 15–30°C (59–86°F) [see USP Controlled Room Temperature].

LAB-0076-16.0
January 2012

PATIENT SUMMARY OF INFORMATION RELPAX® (eletriptan hydrobromide)

Please read this information before you start taking RELPAX and each time you renew your prescription. Remember, this summary does not take the place of discussions with your doctor. You and your doctor should discuss RELPAX when you start taking your medication and at regular checkups.

What is RELPAX?

RELPAX is a prescription medicine used to treat migraine headaches in adults. RELPAX is not for other types of headaches.

What is a Migraine Headache?

Migraine is an intense, throbbing headache. You may have pain on one or both sides of your head. You may have nausea and vomiting, and be sensitive to light and noise. The pain and symptoms of a migraine headache can be worse than a common headache. Some women get migraines around the time of their menstrual period. Some people have visual symptoms before the headache, such as flashing lights or wavy lines, called an aura.

How Does RELPAX Work?

Treatment with RELPAX reduces swelling of blood vessels surrounding the brain. This swelling is associated with the headache pain of a migraine attack. RELPAX blocks the release of substances from nerve endings that cause more pain and other symptoms like nausea, and sensitivity to light and sound.

It is thought that these actions contribute to relief of your symptoms by RELPAX.

Who should not take RELPAX?

Do not take RELPAX if you:

- have uncontrolled high blood pressure.
- have heart disease or a history of heart disease.
- have hemiplegic or basilar migraine (if you are not sure about this, ask your doctor).
- have or had a stroke or problems with your blood circulation.
- have serious liver problems.
- have taken any of the following medicines in the last 24 hours: other "triptans" or triptan combination products such as almotriptan (Axert®), frovatriptan (Frova™), naratriptan (Amerge®), rizatriptan (Maxalt®), sumatriptan (Imitrex®) sumatriptan and naproxen sodium, (Treximet™), zolmitriptan (Zomig®); ergotamines like Bellergal-S®, Cafergot®, Ergomar®, Wigraine®; dihydroergotamine like D.H.E. 45® or Migranal®; or methysergide (Sansert®). These medicines have side effects similar to RELPAX. [The brands listed are the trademarks of their respective owners and are not trademarks of Pfizer Inc.]
- have taken the following medicines within at least 72 hours: ketoconazole (Nizoral®), itraconazole (Sporanox®), nefazodone (Serzone®), troleandomycin (TAO®), clarithromycin (Biaxin®), ritonavir (Norvir®), and nelfinavir (Viracept®). These medicines may cause an increase in the amount of RELPAX in the blood.
- are allergic to RELPAX or any of its ingredients. The active ingredient is eletriptan. The inactive ingredients are listed at the end of this leaflet.

Tell your doctor about all the medicines you take or plan to take, including prescription and non-prescription medicines, supplements, and herbal remedies. Your doctor will decide if you can take RELPAX with your other medicines.

Some medicines used in treating depression such as the selective serotonin reuptake inhibitors (SSRIs) and serotonin norepinephrine reuptake inhibitors (SNRIs) may cause a condition called serotonin syndrome especially during combined use with certain migraine medications. Your doctor needs to know if you are taking any of these medicines, when taking Relpax.

- selective serotonin reuptake inhibitors (SSRIs) or serotonin norepinephrine reuptake inhibitors (SNRIs), two types of drugs for depression or other disorders. Common SSRIs are CELEXA® (citalopram HBr), LEXAPRO® (escitalopram oxalate), PAXIL® (paroxetine), PROZAC®/SARAFEM® (fluoxetine), SYMBYAX® (olanzapine/fluoxetine), ZOLOFT® (sertraline), and fluvoxamine. Common SNRIs are CYMBALTA® (duloxetine) and EFFEXOR® (venlafaxine).

Tell your doctor if you know that you have any of the following: risk factors for heart disease like high cholesterol, diabetes, smoking, obesity, menopause, or a family history of heart disease or stroke.

How should I take RELPAX?

RELPAX comes in 20 mg and 40 mg tablets. When you have a migraine headache, take your medicine as directed by your doctor.

- Take one RELPAX Tablet as soon as you feel a migraine coming on.
- If your headache improves and then comes back after 2 hours, you can take a second tablet.
- If the first tablet did not help your headache at all, do not take a second tablet without talking with your doctor.
- Do not take more than two RELPAX Tablets in any 24-hour period.

What are the possible side effects of RELPAX?

RELPAX is generally well tolerated. As with any medicine, people taking RELPAX may have side effects. The side effects are usually mild and do not last long.

The most common side effects of RELPAX are:

- dizziness
- nausea
- weakness
- tiredness
- pain or pressure sensation (e.g., in the chest or throat)

In very rare cases, patients taking triptans, such as RELPAX, may experience serious side effects, including heart attacks. Call your doctor right away if you have:

- severe chest pains
- shortness of breath

Some patients taking triptans may have a reaction called serotonin syndrome particularly during combined use with certain types of antidepressants, SSRIs or SNRIs. Symptoms may include confusion, hallucinations, fast heart beat, feeling faint, fever, sweating, muscle spasm, difficulty walking and/or diarrhea. Call your doctor right away if you have any of these symptoms after taking RELPAX.

Overuse of anti-migraine drugs like RELPAX can lead to daily headaches. Talk to your doctor if you have persistent non-migraine headaches.

This is not a complete list of side effects. Talk to your doctor if you develop any symptoms that concern you.

What to do in case of an overdose?

Call your doctor or poison control center or go to the ER.

General advice about RELPAX

Medicines are sometimes prescribed for conditions that are not mentioned in patient information leaflets. Do not use RELPAX for a condition for which it was not prescribed. Do not give RELPAX to other people, even if they have the same symptoms you have.

This leaflet summarizes the most important information about RELPAX. If you would like more information about RELPAX, talk with your doctor. You can ask your doctor or pharmacist for information on RELPAX that is written for health professionals. You can also call 1-866-4RELPAX (1-866-473-5729) or visit our web site at www.RELPAX.com.

What are the ingredients in RELPAX?

Active ingredient: eletriptan hydrobromide

Inactive ingredients: microcrystalline cellulose, lactose, croscarmellose sodium, magnesium stearate, titanium oxide, hypromellose, triacetin, and FD&C Yellow No. 6 aluminum lake.

Store RELPAX Tablets at room temperature 15–30°C (59–86°F).

LAB 0077-9.0
January 2012

Relabeling by:

STAT Rx USA LLC

Gainesville, GA 30501